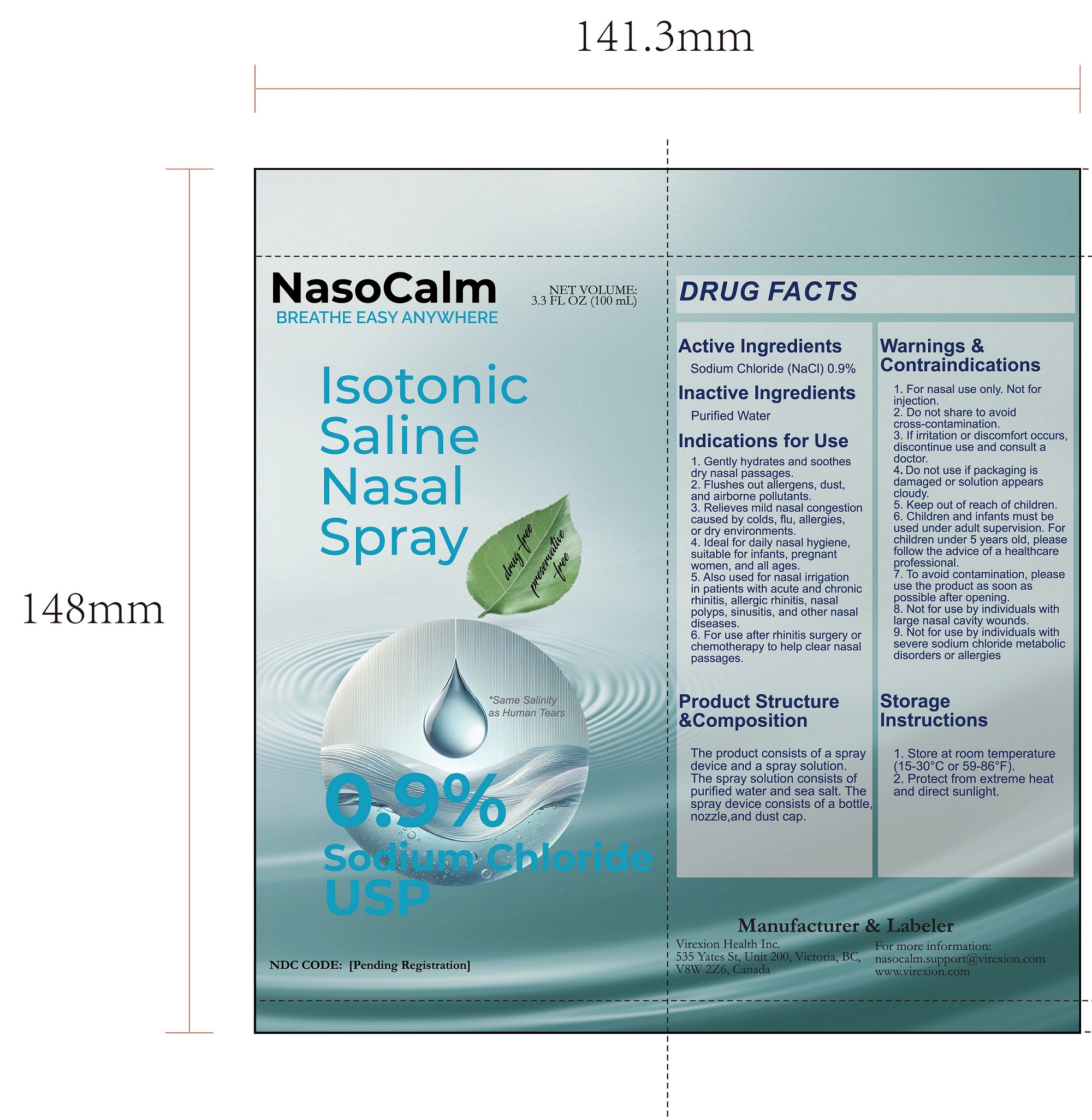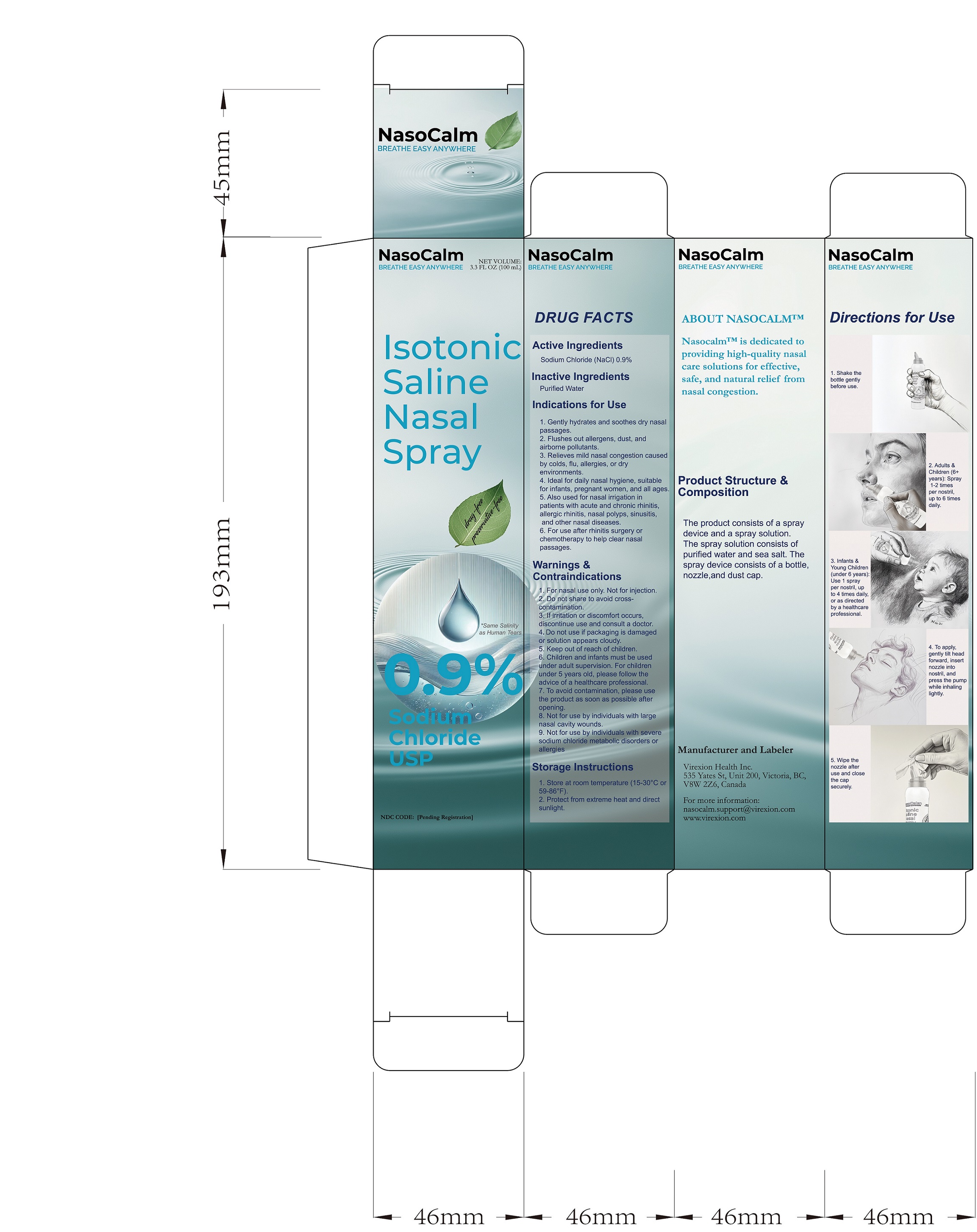 DRUG LABEL: Nasocalm
NDC: 85436-001 | Form: SPRAY
Manufacturer: Virexion Health Inc.
Category: otc | Type: HUMAN OTC DRUG LABEL
Date: 20250319

ACTIVE INGREDIENTS: SODIUM CHLORIDE 0.9 mg/100 mg
INACTIVE INGREDIENTS: WATER

WARNINGS

For nasal use only. Not for injections.
Do not share to avoid cross-contamination.

To avoid contamination, please use the product as soon as possible after opening.

PURPOSE

Hydrates, soothes, and clears nasal passages, relieves mild congestion, and flushes out allergens, dust, and pollutants, suitable for daily nasal hygiene for all ages.

ACTIVE INGREDIENT

Sodium Chloride (NaCl) 0.9%

INDICATIONS AND USAGE

Gently hydrates and soothes dry nasal passages.
Flushes out allergens, dust, and airborne pollutants.
Relieves mild nasal congestion caused by colds, flu, allergies, or dry environments.
Ideal for daily nasal hygiene, suitable for infants, pregnant women, and all ages.
Also used for nasal irrigation in patients with acute and chronic rhinitis, allergic rhinitis, nasal polyps, sinusitis, and other nasal diseases.
For use after rhinitis surgery or chemotherapy to help clear nasal passages.

DO NOT USE

If irritation or discomfort occurs, discontinue use and consult a doctor.
Do not use if packaging is damaged or solution appears cloudy.
Not for use by individuals with large nasal cavity wounds.
Not for use by individuals with severe sodium chloride metabolic disorders or allergies.

Keep out of reach of children.

Directions

1. Shake the bottle gently before use.

2. Adults & Children (6+ years): Spray 1-2 times per nostril, up to 6 times daily.

3. Infants & Young Children (under 6 years): Use 1 spray per nostril, up to 4 times daily, or as directed by a healthcare professional.

4. To apply, gently tilt head forward, insert nozzle into nostril, and press the pump while inhaling lightly.

5. Wipe the nozzle after use and close the cap securely.

6. Children and infants must be used under adult supervision. For children under 5 years old, please follow the advice of a healthcare professional.

STORAGE AND HANDLING

1. Store at room temperature (15-30°C or 59-86°F).

2. Protect from extreme heat and direct sunlight.

INACTIVE INGREDIENT

Purified water USP